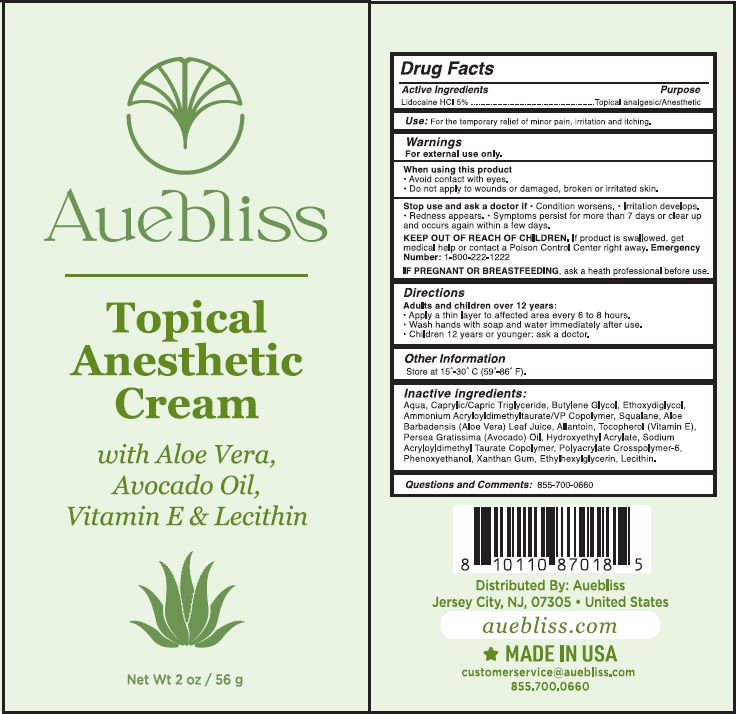 DRUG LABEL: Auebliss
NDC: 73143-002 | Form: CREAM
Manufacturer: Jag Alliance, LLC
Category: otc | Type: HUMAN OTC DRUG LABEL
Date: 20230105

ACTIVE INGREDIENTS: LIDOCAINE 5 g/100 g
INACTIVE INGREDIENTS: WATER; BUTYLENE GLYCOL; DIETHYLENE GLYCOL MONOETHYL ETHER; AMMONIUM ACRYLOYLDIMETHYLTAURATE/VP COPOLYMER; SQUALANE; ALOE VERA LEAF; ALLANTOIN; TOCOPHEROL; AVOCADO OIL; 2-HYDROXYETHYL ACRYLATE; HYDROXYETHYL ACRYLATE/SODIUM ACRYLOYLDIMETHYL TAURATE COPOLYMER (100000 MPA.S AT 1.5%); AMMONIUM ACRYLOYLDIMETHYLTAURATE, DIMETHYLACRYLAMIDE, LAURYL METHACRYLATE AND LAURETH-4 METHACRYLATE COPOLYMER, TRIMETHYLOLPROPANE TRIACRYLATE CROSSLINKED (45000 MPA.S); PHENOXYETHANOL; XANTHAN GUM; ETHYLHEXYLGLYCERIN; LECITHIN, SOYBEAN; TRICAPRIN

Active Ingredient

Lidocaine HCl 5%

Purpose

Topical analgesic/Anesthetic

Uses

For the temporary relief of minor pain, irritation and itching

Warnings

For external use only.
When using this product Avoid contact with eyes.
Do not apply to wounds or damaged, broken or irritated skin
Stop use and ask a doctor If• Condition worsens. • Irritation develops. Redness appears. • Symptoms persist for more than 7 days or clear up and occurs again within a few days.

Keep out of reach of children If product is swallowed, get medical help or contact a Poison Control Center right away. Emergency Number: 1-800-222-1222

IF PREGNANT OR BREASTFEEDING, ask a heath professional before use

Directions

Adults and children over 12 years:
• Apply a thin layer to affected area every 6 to 8 hours.
• Wash hands with soap and water immediately after use.
• Children 12 years or younger: ask a doctor.

Other Information

Store at 15•-30• C (59'-86' F).

Inactive ingredients

Aqua, Caprylic/Capric Triglyceride, Butylene Glycol, Ethoxydiglycol, Ammonium AcryloyldimethyltaurateNP Copolymer, Squalane, Aloe Barbadensis (Aloe Vera) Leaf Juice, Allantoin, Tocopherol (Vitamin E), Persea Gratissima (Avocado) Oil, Hydroxyethyl Acrylate, Sodium Acryloyldimethyl Tau rate Copolymer, Polyacrylate Crosspolymer-6, Phenoxyethanol, Xanthan Gum, Ethylhexylglycerin, Lecithin.

Questions and comments

855-700-0660